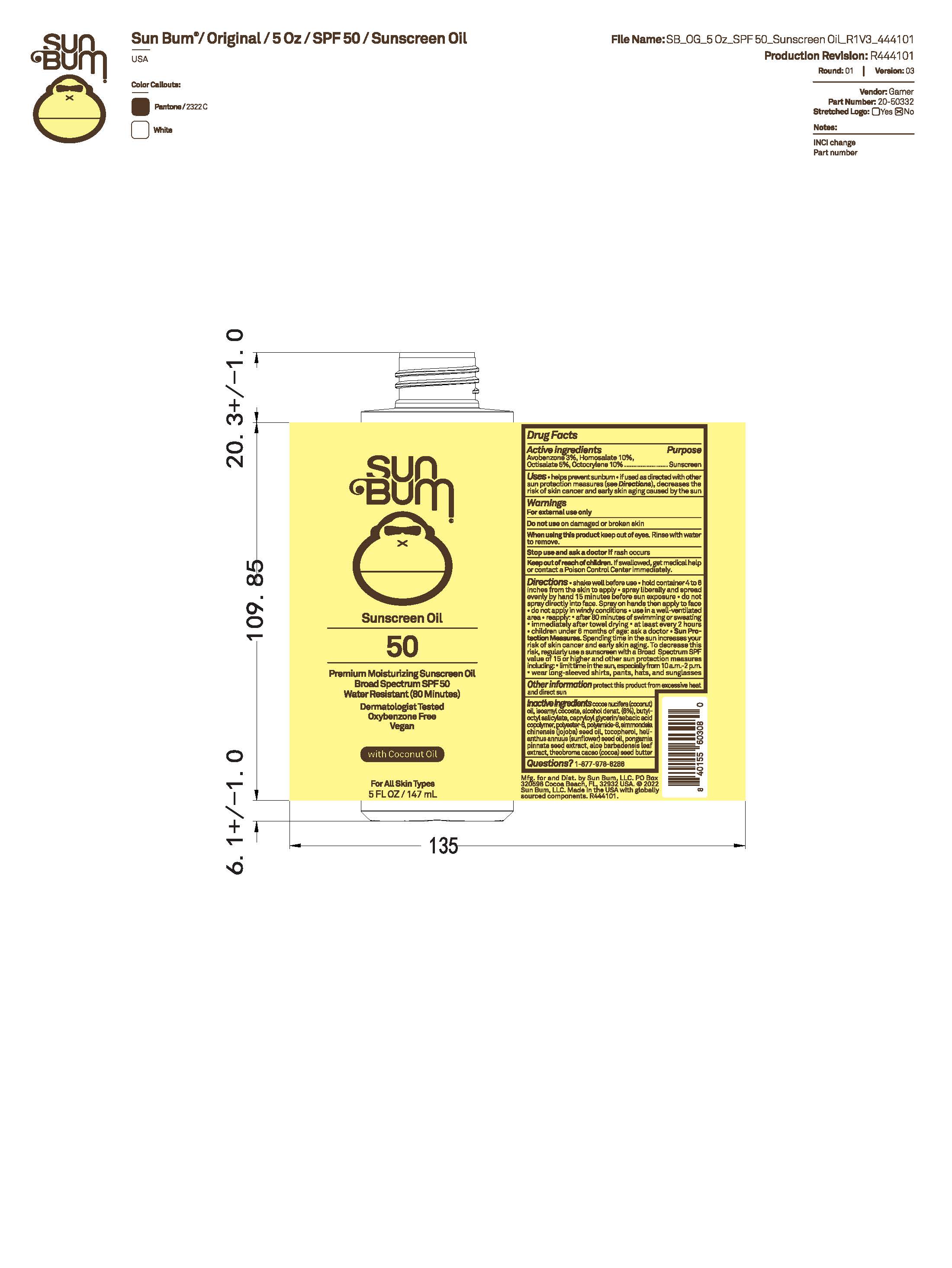 DRUG LABEL: Sun Bum Sunscreen Oil 50 5 OZ
NDC: 69039-765 | Form: OIL
Manufacturer: Sun Bum, LLC
Category: otc | Type: HUMAN OTC DRUG LABEL
Date: 20250818

ACTIVE INGREDIENTS: AVOBENZONE 30 mg/1 mL; OCTISALATE 50 mg/1 mL; OCTOCRYLENE 100 mg/1 mL; HOMOSALATE 100 mg/1 mL
INACTIVE INGREDIENTS: THEOBROMA CACAO (COCOA) SEED BUTTER; POLYAMIDE-8 (4500 MW); BUTYLOCTYL SALICYLATE; PONGAMOL; ISOAMYL COCOATE; TOCOPHEROL; COCOS NUCIFERA (COCONUT) OIL; HELIANTHUS ANNUUS (SUNFLOWER) SEED OIL; ALOE BARBADENSIS LEAF; POLYESTER-8 (1400 MW, CYANODIPHENYLPROPENOYL CAPPED); SIMMONDSIA CHINENSIS (JOJOBA) SEED OIL; CAPRYLOYL GLYCERIN/SEBACIC ACID COPOLYMER (2000 MPA.S); ALCOHOL

Sun Bum Sunscreen Oil 50 5 OZ

Active Ingredients

Homosalate 10.0
Octocrylene 10.0
Octisalate 5.0
Avobenzone 3.0

Purpose

Sunscreen

Uses

• helps prevent sunburn • if used as directed with other sun protection measures, (see Directions) decreases the risk of skin cancer and early skin aging caused by the sun

Warnings

For external use only

Do not use on damaged or broken skin

When using this product keep out of eyes. Rinse with water to remove.

Stop use and ask a doctor if rash occurs

Keep out of reach of children. If swallowed, get medical help or contact a Poison Control Center immediately.

Warnings

Keep Out Of Reach Of Children

Directions

• shake well before use

• hold container 4 to 6 inches from the skin to apply

• spray liberally and spread evenly by hand 15 minutes before sun exposure

• do not spray directly onto face. Spray on hands then apply to face.

• do not apply in windy conditions

• use in a well-ventilated area

•Avoid inhaling or exposing others to spray

• reapply: after 80 minutes of swimming or sweating

• immediately after towel drying

• at least every 2 hours

• children under 6 months of age: ask a doctor

• Sun Protection Measures. Spending time in the sun increases your risk of skin cancer and early skin aging. To decrease this risk, regularly use a sunscreen with a Broad Spectrum SPF value of 15 or higher and other sun protection measures including:

• limit time in the sun, especially from 10 a.m.- 2 p.m.

• wear long-sleeved shirts, pants, hats and sunglasses

Directions

• shake well before use

• hold container 4 to 6 inches from the skin to apply

• spray liberally and spread evenly by hand 15 minutes before sun exposure

• do not spray directly onto face. Spray on hands then apply to face.

• do not apply in windy conditions

• use in a well-ventilated area

•Avoid inhaling or exposing others to spray

Other Information

protect this product from excessive heat and direct sun

Inactive ingredients

cocos nucifera (coconut) oil, isoamyl cocoate, alcohol denat. (6%), butyloctyl salicylate, capryloyl glycerin/sebacic acid copolymer, polyester-8, polyamide-8, simmondsia chinensis (jojoba) seed oil, tocopherol, helianthus annuus (sunflower) seed oil, pongamol, aloe barbadensis leaf extract, theobroma cacao (cocoa) seed butter

Questions?

1-877-978-6286